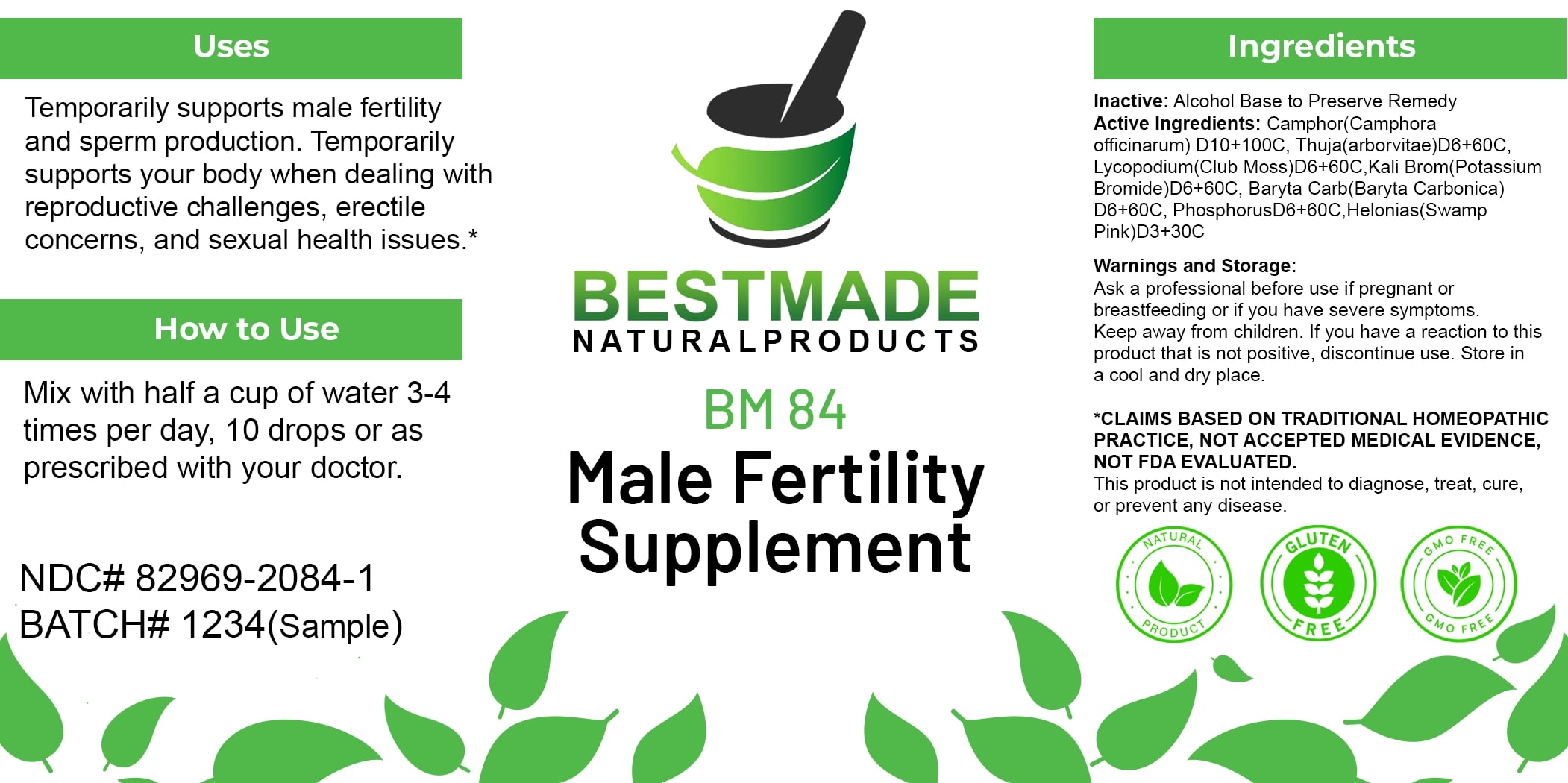 DRUG LABEL: Bestmade Natural Products BM84
NDC: 82969-2084 | Form: LIQUID
Manufacturer: Bestmade Natural Products
Category: homeopathic | Type: HUMAN OTC DRUG LABEL
Date: 20250131

ACTIVE INGREDIENTS: CINNAMOMUM CAMPHORA WHOLE 30 [hp_C]/30 [hp_C]; BARIUM CARBONATE 30 [hp_C]/30 [hp_C]; PHOSPHORUS 30 [hp_C]/30 [hp_C]; CHAMAELIRIUM LUTEUM ROOT 30 [hp_C]/30 [hp_C]; LYCOPODIUM CLAVATUM SPORE 30 [hp_C]/30 [hp_C]; POTASSIUM BROMIDE 30 [hp_C]/30 [hp_C]; THUJA OCCIDENTALIS LEAFY TWIG 30 [hp_C]/30 [hp_C]
INACTIVE INGREDIENTS: ALCOHOL 30 [hp_C]/30 [hp_C]

BM84

DOSAGE AND ADMINISTRATION

How to Use

Mix with half a cup of water 3-4 times per day, 10 drops or as prescribed with your doctor.

INACTIVE INGREDIENT

How to Use

Mix with half a cup of water 3-4 times per day, 10 drops or as prescribed with your doctor.

ACTIVE INGREDIENT

Active Ingredients: Camphor(Camphora officinarum)D10+100C, Thuja(arborvitae)D6+60C, Lycopodium(Club Moss)D6+60C, Kali Brom(Potassium Bromide)D6+60C, Baryta Carb(Baryta Carbonica) D6+60C, PhosphorusD6+60C, Helonias(Swamp Pink)D3+30C

Uses

Temporarily supports male fertility and sperm production. Temporarily supports your body when dealing with reproductive challenges, erectile concerns, and sexual health issues.*

*CLAIMS BASED ON TRADITIONAL HOMEOPATHIC PRACTICE, NOT ACCEPTED MEDICAL EVIDENCE, NOT FDA EVALUATED.

This product is not intended to diagnose, treat, cure, or prevent any disease.

Uses

Temporarily supports male fertility and sperm production. Temporarily supports your body when dealing with reproductive challenges, erectile concerns, and sexual health issues.*

*CLAIMS BASED ON TRADITIONAL HOMEOPATHIC PRACTICE, NOT ACCEPTED MEDICAL EVIDENCE, NOT FDA EVALUATED.

This product is not intended to diagnose, treat, cure, or prevent any disease.

KEEP OUT OF REACH OF CHILDREN

Warnings and Storage:

Ask a professional before use if pregnant or breastfeeding or if you have severe symptoms. Keep away from children. If you have a reaction to this product that is not positive, discontinue use. Store in a cool and dry place.

Warnings and Storage:

Ask a professional before use if pregnant or breastfeeding or if you have severe symptoms. Keep away from children. If you have a reaction to this product that is not positive, discontinue use. Store in a cool and dry place.

*CLAIMS BASED ON TRADITIONAL HOMEOPATHIC PRACTICE, NOT ACCEPTED MEDICAL EVIDENCE, NOT FDA EVALUATED.

This product is not intended to diagnose, treat, cure, or prevent any disease.

Entire package label